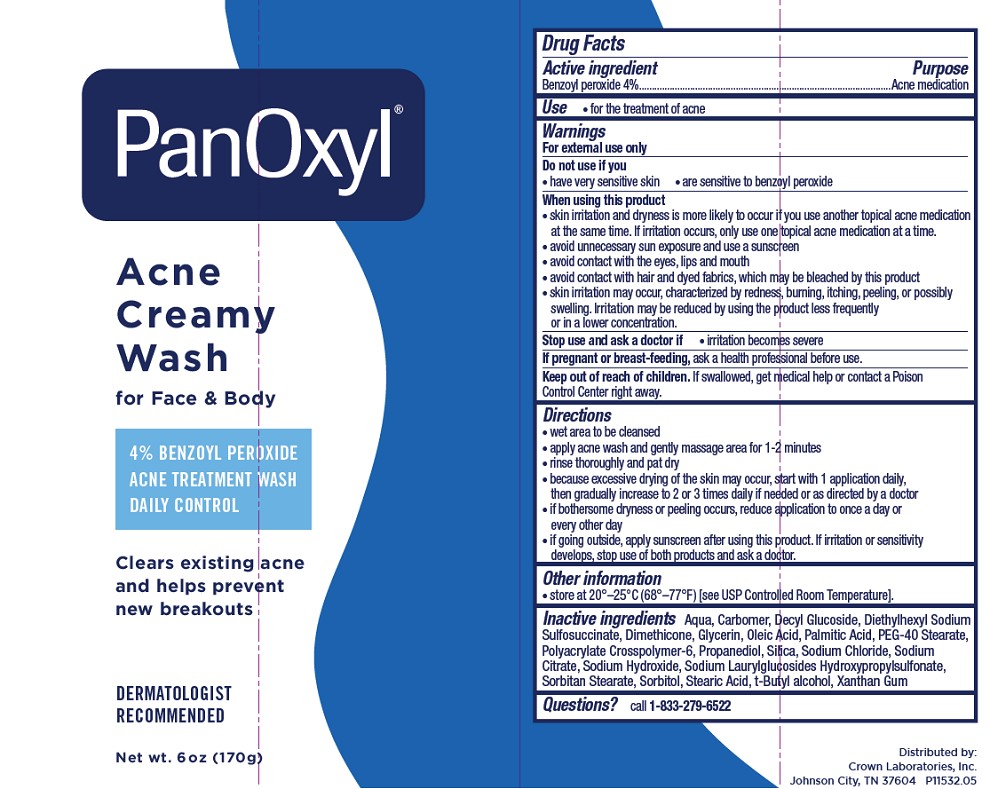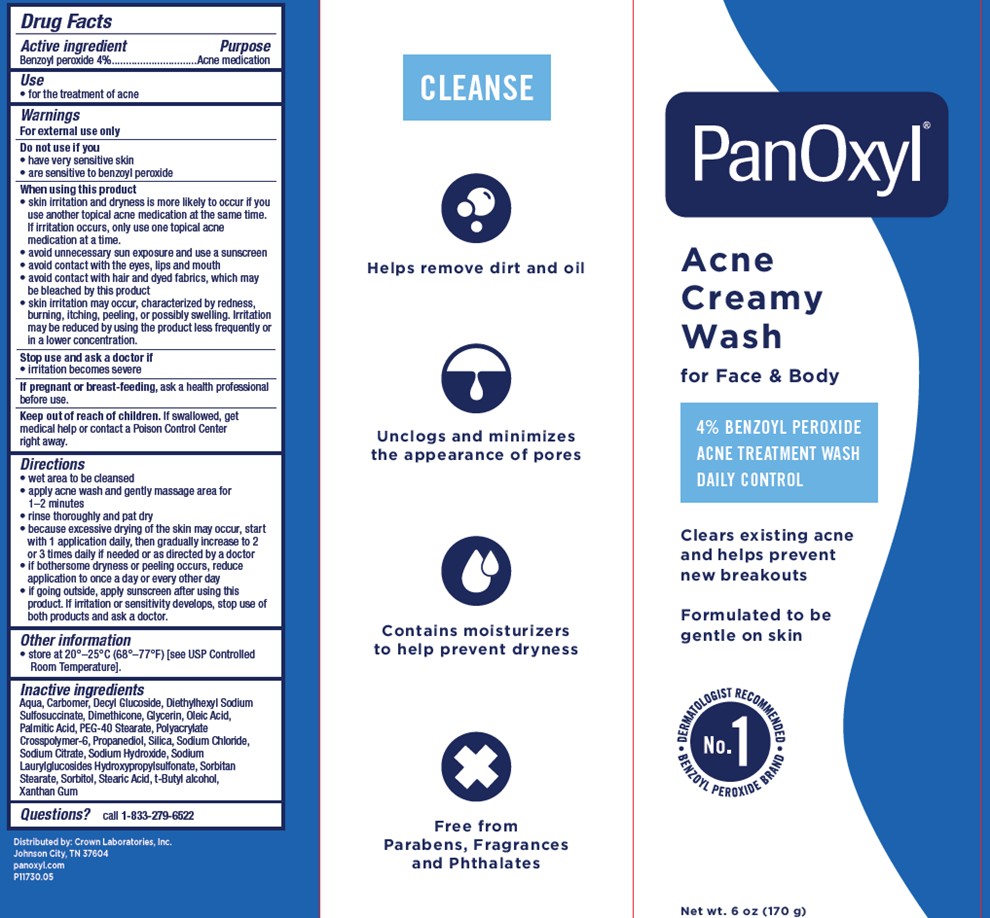 DRUG LABEL: PanOxyl
NDC: 0316-0227 | Form: CREAM
Manufacturer: Crown Laboratories
Category: otc | Type: HUMAN OTC DRUG LABEL
Date: 20260112

ACTIVE INGREDIENTS: BENZOYL PEROXIDE 58.7 mg/1 g
INACTIVE INGREDIENTS: XANTHAN GUM; CARBOMER INTERPOLYMER TYPE A (ALLYL SUCROSE CROSSLINKED); DIMETHICONE; DOCUSATE SODIUM; PALMITIC ACID; SODIUM CITRATE; SODIUM CHLORIDE; TERT-BUTYL ALCOHOL; SORBITAN MONOSTEARATE; SILICON DIOXIDE; WATER; AMMONIUM ACRYLOYLDIMETHYLTAURATE, DIMETHYLACRYLAMIDE, LAURYL METHACRYLATE AND LAURETH-4 METHACRYLATE COPOLYMER, TRIMETHYLOLPROPANE TRIACRYLATE CROSSLINKED (45000 MPA.S); SORBITOL; GLYCERIN; DECYL GLUCOSIDE; STEARIC ACID; CARBOMER HOMOPOLYMER TYPE C (ALLYL PENTAERYTHRITOL CROSSLINKED); SODIUM HYDROXIDE; POLYOXYL 40 STEARATE; PROPANEDIOL

Panoxyl Acne Creamy Wash

Active ingredient

Benzoyl peroxide 4%

Purpose

Acne medication

Use

- for the treatment of acne

Warnings

For external use only

Do not use if you

- have very sensitive skin
- are sensitive to benzoyl peroxide

When using this product

- skin irritation and dryness is more likely to occur if you use another topical acne medication at the same time. If irritation occurs, only use one topical acne medication at a time
- avoid unnecessary sun exposure and use a sunscreen
- avoid contact with the eyes, lips and mouth
- avoid contact with hair and dyed fabrics, which may be bleached by this product
- skin irritation may occur, characterized by redness, burning, itching, peeling, or possibly swelling. Irritation may be reduced by using the product less frequently or in a lower concentration.

Stop use and ask a doctor if

- irritation becomes severe

If pregnant or breast-feeding,

ask a health professional before use.

Keep out of reach of children.

If swallowed, get medical help or contact a Poison Control Center right away.

Directions

- wet area to be cleansed
- apply acne wash and gently massage area for 1-2 minutes
- rinse thoroughly and pat dry
- because excessive drying of the skin may occur, start with 1 application daily, then gradually increase to 2 or 3 times daily if needed or as directed by a doctor
- if bothersome dryness or peeling occurs, reduce application to once a day or every other day
- if going outside, apply sunscreen after using this product. If irritation or sensitivity develops, stop use of both products and ask a doctor.

Other information

- Store at 20o - 25oC (68o - 77oF) [see USP Controlled Room Temperature].

Inactive ingredients (4%)

Aqua, Carbomer, Decyl Glucoside, Diethylhexyl Sodium Sulfosuccinate, Dimethicone, Glycerin, Oleic Acid, Palmitic Acid, PEG-40 Stearate, Polyacrylate Crosspolymer-6, Propanediol, Silica, Sodium Chloride, Sodium Citrate, Sodium Hydroxide, Sodium Laurylglucosides Hydroxypropylsulfonate, Sorbitan Stearate, Sorbitol, Stearic Acid, t-Butyl alcohol, Xanthan Gum

Questions or comments?

call 1-833-279-6522

Panoxyl 4% Tube

PanOxyl®

ACNE CREAMY WASH

for Face & Body

4% Benzoyl Peroxide

Acne Treatment Wash

Daily Control

Clears existing acne and helps prevent new breakouts

Net wt. 6oz (170g)

Panoxyl 4% Carton

PanOxyl®

ACNE CREAMY WASH

for Face & Body

4% Benzoyl Peroxide

Acne Treatment

Daily Control

Clears existing acne and helps prevent new breakouts

Formulated to be genlt on skin

Net wt. 6oz (170g)